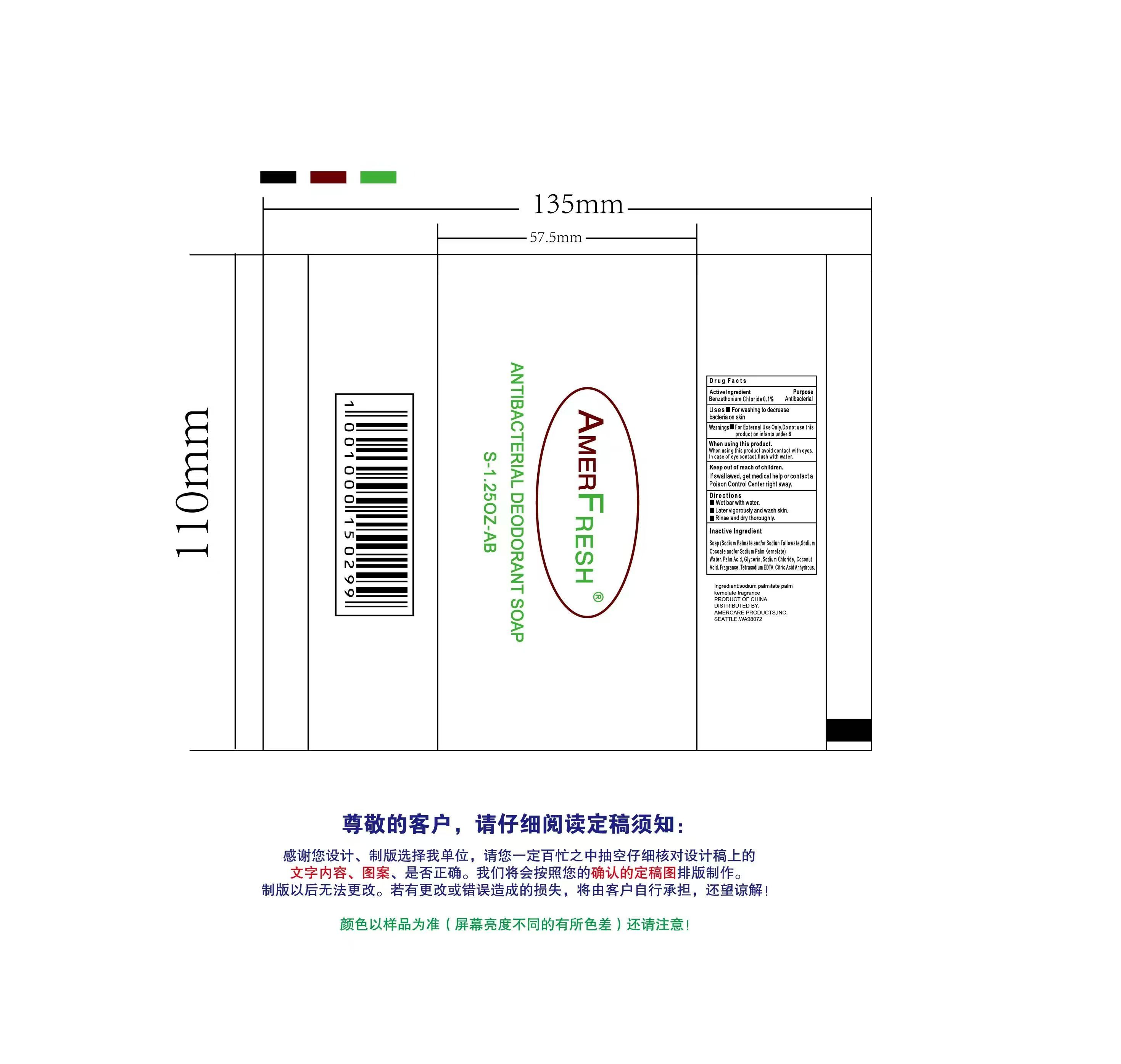 DRUG LABEL: Amerfresh Antibacterial Deodorant
NDC: 85420-002 | Form: SOAP
Manufacturer: Liufangjing Biotechnology (Yangzhou) Co., Ltd
Category: otc | Type: HUMAN OTC DRUG LABEL
Date: 20250909

ACTIVE INGREDIENTS: BENZETHONIUM CHLORIDE 0.1 g/100 g
INACTIVE INGREDIENTS: WATER; SODIUM PALM KERNELATE; PALM ACID; SODIUM PALMATE; SODIUM CHLORIDE; GLYCERIN; COCONUT ACID; EDETATE SODIUM; CITRIC ACID MONOHYDRATE; SODIUM TALLOWATE; SODIUM COCOATE

85420-002 Amber Fresh Antibacterial deodorant Soap

Active Ingredient

Benzethonium Chloride 0.1%

Purpose

Antibacterial

Use

For washing to decrease bacteria on skin

Warnings

For external use only

Do not use this product on infants under 6

When using this product avoid contact with eyes. In case of eye contact flush with water

Keep out of reach of children. If swallowed, get medical help or contact a Poison Control Center right away.

Directions

Wet bar with water

Lather vigorously and wash skin

Rinse and dry thoroughly

Inactive ingredients

Soap (Sodium Palmate and/or Sodium Tallowate, Sodium Cocoate and/or Sodium Palm Kernelate), Water, Palm Acid, Glycerin, Coconut Acid, Fragrance, tetrasodium EDTA, Citric Acid Anhydrous